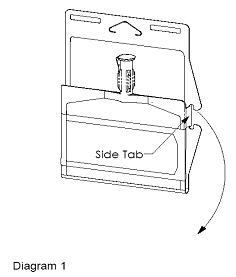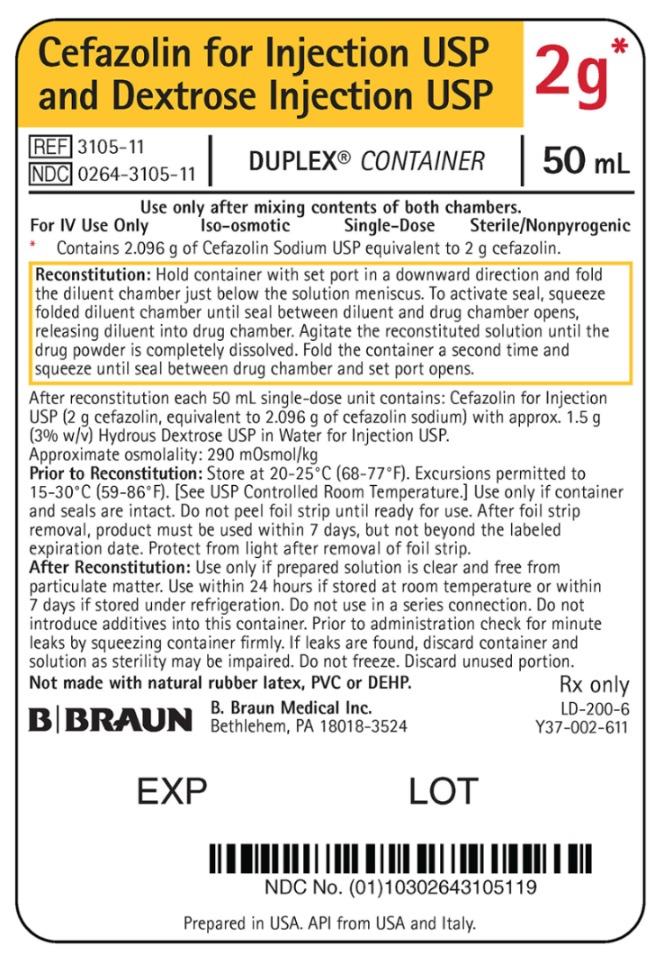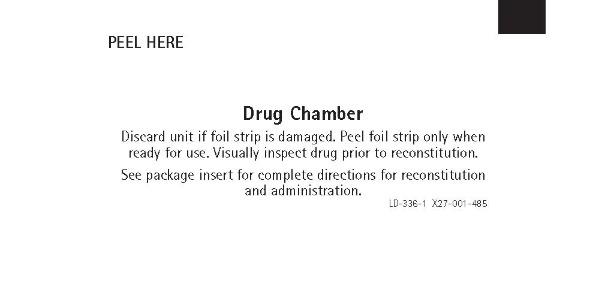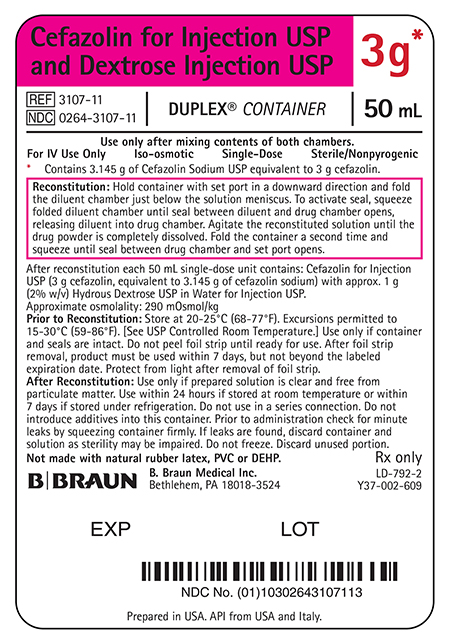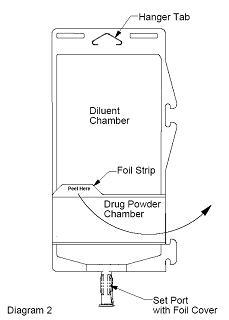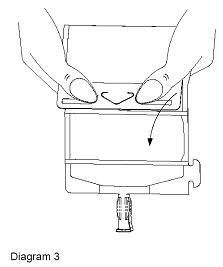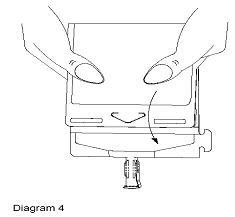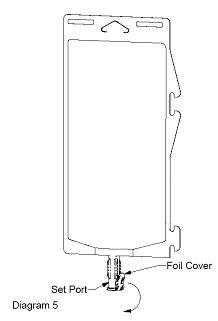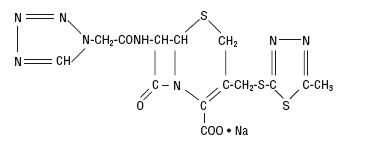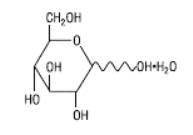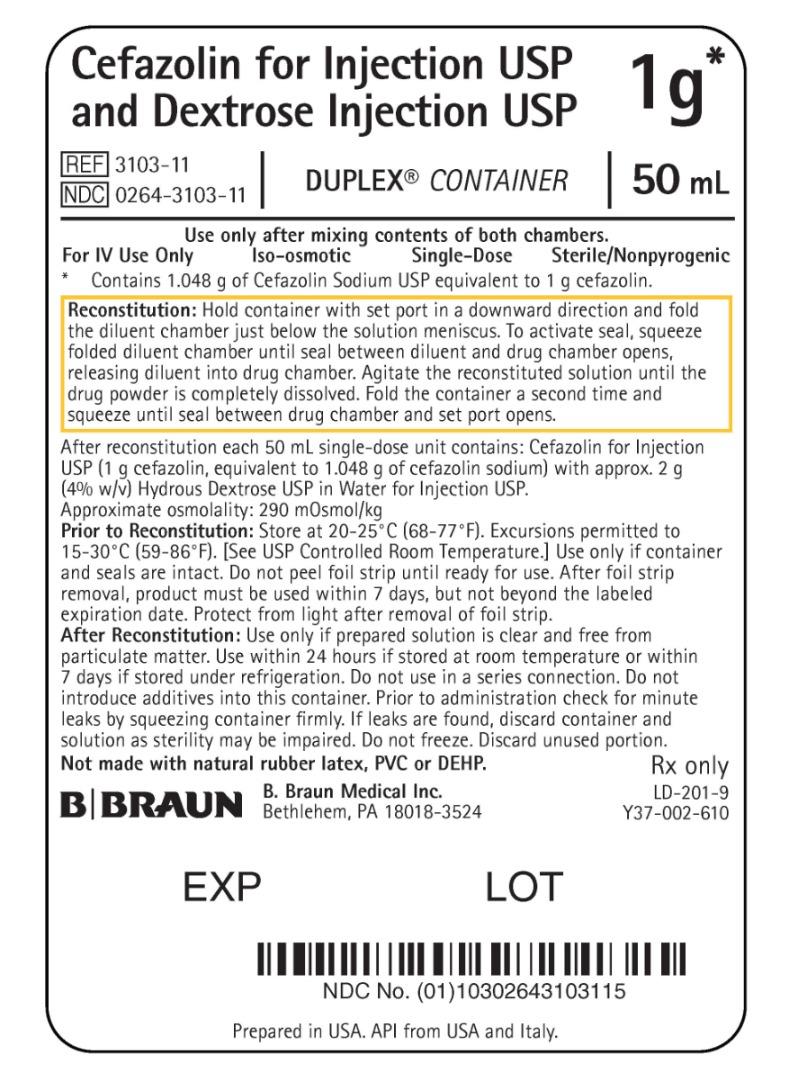 DRUG LABEL: Cefazolin Sodium
NDC: 0264-3103 | Form: SOLUTION
Manufacturer: B. Braun Medical Inc.
Category: prescription | Type: HUMAN PRESCRIPTION DRUG LABEL
Date: 20250310

ACTIVE INGREDIENTS: CEFAZOLIN SODIUM 1 g/50 mL
INACTIVE INGREDIENTS: DEXTROSE MONOHYDRATE 2 g/50 mL; WATER

HIGHLIGHTS OF PRESCRIBING INFORMATION

These highlights do not include all the information needed to use CEFAZOLIN FOR INJECTION AND DEXTROSE INJECTION safely and effectively. See full prescribing information for CEFAZOLIN FOR INJECTION AND DEXTROSE INJECTION.
CEFAZOLIN FOR INJECTION AND DEXTROSE INJECTION, for intravenous use
Initial U.S. Approval: 1973

RECENT MAJOR CHANGES

Dosage and Administration, Dosage for Perioperative Prophylaxis (2.3) 8/2024

Warnings and Precautions, Prothrombin Activity (5.5) 8/2024

1 INDICATIONS AND USAGE

Cefazolin for Injection and Dextrose Injection is a cephalosporin antibacterial indicated for:

- Treatment of the following infections caused by susceptible isolates of the designated microorganisms in adult and pediatric patients for whom appropriate dosing with this formulation can be achieved: (1)

- Respiratory tract infections (1.1)
- Urinary tract infections (1.2)
- Skin and skin structure infections (1.3)
- Biliary tract infections (1.4)
- Bone and joint infections (1.5)
- Genital infections (1.6)
- Septicemia (1.7)
- Endocarditis (1.8)

- Perioperative prophylaxis in adults and pediatric patients aged
  10 to 17 years old for whom appropriate dosing with this formulation can be achieved (1.9)

To reduce the development of drug-resistant bacteria and maintain the effectiveness of Cefazolin for Injection and Dextrose Injection and other antibacterial drugs, Cefazolin for Injection and Dextrose Injection should be used only to treat or prevent infections that are proven or strongly suspected to be caused by bacteria. (1.10).

2 DOSAGE AND ADMINISTRATION

If a dose of Cefazolin for Injection and Dextrose Injection is required that does not equal 1 gram, 2 grams or 3 grams, this product is not recommended for use and an alternative formulation of cefazolin should be considered. (2.1)

For intravenous use only administered over approximately 30 minutes. (2.1)

Recommended Dosing Schedule in Adult Patients with CLcr Greater Than or Equal To 55 mL/min. (2.1, 2.2 and 2.3)
Site and Type of Infection | Dose | Frequency
Moderate to severe infections | 500 milligram (mg) to 1 gram | every 6 to 8 hours
Mild infections caused by susceptible gram-positive cocci | 250 mg to 500 mg | every 8 hours
Acute, uncomplicated urinary tract infections | 1 gram | every 12 hours
Pneumococcal pneumonia | 500 mg | every 12 hours
Severe, life-threatening infections (e.g., endocarditis, septicemia) [In rare instances, doses of up to 12 grams of cefazolin per day have been used.] | 1 gram to 1.5 grams | every 6 hours
Perioperative prophylaxis | less than 120 kg: 1 gram to 2 grams | 1/2 to 1 hour prior to start of surgery
Perioperative prophylaxis | greater than or equal to 120 kg: 3 grams | 1/2 to 1 hour prior to start of surgery
Perioperative prophylaxis | 500 mg to 1 gram | additional dose during lengthy operative procedures
Perioperative prophylaxis | 500 mg to 1 gram | every 6 to 8 hours for 24 hours postoperatively

Recommended Dosing Schedule in Pediatric Patients with CLcr Greater than or Equal to 70 mL/min. (2.1, 2.2, and 2.3)
Site and Type of Infection | Dose | Frequency
Moderate to severe infections [For the treatment indications (1.1 to 1.8)] | 25 to 50 mg per kilogram (kg) | divided into 3 or 4 equal doses
Severe infections | May increase to 100 mg per kg | divided into 3 or 4 equal doses
Perioperative prophylaxis (10 to 17 years old) | less than 50 kg: 1 gram | 1/2 to 1 hour prior to start of surgery
Perioperative prophylaxis (10 to 17 years old) | greater than or equal to 50 kg: 2 grams | 1/2 to 1 hour prior to start of surgery
Perioperative prophylaxis (10 to 17 years old) | 500 mg to 1 gram | Additional dose during lengthy operative procedures
Perioperative prophylaxis (10 to 17 years old) | 500 mg to 1 gram | every 6 to 8 hours for 24 hours postoperatively

- Dosage adjustment is required for adult patients with CLcr that is less than 55 mL/min and pediatric patients with CLcr that is less than 70 mL/min. (2.4 and 8.6)
- See full prescribing information for preparation and administration instructions. (2.5)

3 DOSAGE FORMS AND STRENGTHS

Dual-Chamber in single-dose Duplex® Container:

- 1 gram Cefazolin for Injection USP and 50 mL 4% Dextrose Injection USP (3)
- 2 grams Cefazolin for Injection USP and 50 mL 3% Dextrose Injection USP (3)
- 3 grams Cefazolin for Injection USP and 50 mL 2% Dextrose Injection USP (3)

4 CONTRAINDICATIONS

- Hypersensitivity to cefazolin or other cephalosporin class antibacterial drugs, penicillins, or other beta-lactams (4.1)

5 WARNINGS AND PRECAUTIONS

- Hypersensitivity reactions: Cross-hypersensitivity may occur in up to 10% of patients with a history of penicillin allergy. If an allergic reaction occurs, discontinue the drug. (5.1)
- Clostridioides difficile-associated Diarrhea (CDAD): May range from mild diarrhea to fatal colitis. Evaluate if diarrhea occurs. (5.3)
- Prothrombin Activity: May be associated with a fall in prothrombin activity. Prothrombin time should be monitored in patients at risk and exogenous vitamin K administered as indicated (5.5)

6 ADVERSE REACTIONS

- Adult and Pediatric Patients: Most common adverse reactions: gastrointestinal (nausea, vomiting, diarrhea), and allergic reactions (anaphylaxis, urticaria, skin rash). (6)
- Pediatric Patients with Perioperative Prophylaxis: The most frequently reported adverse reactions (incidence ≥ 5%) were nausea, infusion site pain, and headache. (6)

To report SUSPECTED ADVERSE REACTIONS, contact B. Braun Medical Inc. at 1-800-854-6851 or FDA at 1-800-FDA-1088 or www.fda.gov/medwatch.

7 DRUG INTERACTIONS

- Probenecid: The renal excretion of cefazolin is inhibited by probenecid. Co-administration of probenecid with cefazolin for injection is not recommended. (7)

FULL PRESCRIBING INFORMATION

RECENT MAJOR CHANGES

Indications and Usage, Perioperative Prophylaxis (1.9) 12/2019

Dosage and Administration, Dosage for Treatment of Indicated Infections in Pediatric Patients (2.3) 12/2019

Dosage and Administration, Dosage for Perioperative Prophylactic Use in Pediatric Patients Aged 10 to 17 (2.4) 12/2019

Dosage and Administration, Dosage in Pediatric Patients with Renal Impairment (2.6) 12/2019

1 INDICATIONS AND USAGE

1.1 Respiratory Tract Infections

Cefazolin for Injection and Dextrose Injection is indicated for the treatment of respiratory tract infections due to Streptococcus pneumoniae, Staphylococcus aureus and Streptococcus pyogenes in adults and pediatric patients for whom appropriate dosing with this formulation can be achieved [see Dosage and Administration (2.1, 2.2, 2.4, 2.5) and Use in Specific Populations (8.4)].

Limitations of Use

Injectable benzathine penicillin is considered the drug of choice in treatment and prevention of streptococcal infections, including the prophylaxis of rheumatic fever.

Cefazolin for Injection and Dextrose Injection is indicated for the eradication of streptococci from the nasopharynx; however, data establishing the efficacy of cefazolin in the subsequent prevention of rheumatic fever are not available.

1.2 Urinary Tract Infections

Cefazolin for Injection and Dextrose Injection is indicated for the treatment of urinary tract infections due to Escherichia coli, and Proteus mirabilis in adults and pediatric patients for whom appropriate dosing with this formulation can be achieved [see Dosage and Administration (2.1, 2.2, 2.4, 2.5) and Use in Specific Populations (8.4)].

1.3 Skin and Skin Structure Infections

Cefazolin for Injection and Dextrose Injection is indicated for the treatment of skin and skin structure infections due to S. aureus, S. pyogenes, and Streptococcus agalactiae in adults and pediatric patients for whom appropriate dosing with this formulation can be achieved [see Dosage and Administration (2.1, 2.2, 2.4, 2.5) and Use in Specific Populations (8.4)].

1.4 Biliary Tract Infections

Cefazolin for Injection and Dextrose Injection is indicated for the treatment of biliary infections due to E. coli, various isolates of streptococci, P. mirabilis, and S. aureus in adults and pediatric patients for whom appropriate dosing with this formulation can be achieved [see Dosage and Administration (2.1, 2.2, 2.4, 2.5) and Use in Specific Populations (8.4)].

1.5 Bone and Joint Infections

Cefazolin for Injection and Dextrose Injection is indicated for the treatment of bone and joint infections due to S. aureus in adults and pediatric patients for whom appropriate dosing with this formulation can be achieved [see Dosage and Administration (2.1, 2.2, 2.4, 2.5) and Use in Specific Populations (8.4)].

1.6 Genital Infections

Cefazolin for Injection and Dextrose Injection is indicated for the treatment of genital infections due to E. coli, and P. mirabilis in adults and pediatric patients for whom appropriate dosing with this formulation can be achieved [see Dosage and Administration (2.1, 2.2, 2.4, 2.5) and Use in Specific Populations (8.4)].

1.7 Septicemia

Cefazolin for Injection and Dextrose Injection is indicated for the treatment of septicemia due to S. pneumoniae, S. aureus, P. mirabilis, and E. coli in adults and pediatric patients for whom appropriate dosing with this formulation can be achieved [see Dosage and Administration (2.1, 2.2, 2.4, 2.5) and Use in Specific Populations (8.4)].

1.8 Endocarditis

Cefazolin for Injection and Dextrose Injection is indicated for the treatment of endocarditis due to S. aureus and S. pyogenes in adults and pediatric patients for whom appropriate dosing with this formulation can be achieved [see Dosage and Administration (2.1, 2.2, 2.4, 2.5) and Use in Specific Populations (8.4)].

1.9 Perioperative Prophylaxis

Cefazolin for Injection and Dextrose Injection is indicated for perioperative prophylaxis in adults and pediatric patients aged 10 to 17 years old for whom appropriate dosing with this formulation can be achieved [see Dosage and Administration (2.1, 2.3, 2.4, 2.5) and Use in Specific Populations (8.4)].

The perioperative use of Cefazolin for Injection and Dextrose Injection is indicated in adult and pediatric (aged 10 to 17 years old) surgical patients in whom infection at the operative site would present a serious risk (e.g., during open-heart surgery and prosthetic arthroplasty).

The prophylactic administration of Cefazolin for Injection and Dextrose Injection preoperatively, intraoperatively, and postoperatively may reduce the incidence of certain postoperative infections in patients undergoing surgical procedures which are classified as contaminated or potentially contaminated (e.g., vaginal hysterectomy, and cholecystectomy in high-risk patients such as those older than 70 years, with acute cholecystitis, obstructive jaundice, or common duct bile stones).

1.10 Usage

To reduce the development of drug-resistant bacteria and maintain the effectiveness of Cefazolin for Injection and Dextrose Injection and other antibacterial drugs, Cefazolin for Injection and Dextrose Injection should be used only to treat or prevent infections that are proven or strongly suspected to be caused by susceptible bacteria. When culture and susceptibility information are available, they should be considered in selecting or modifying antibacterial therapy. In the absence of such data, local epidemiology and susceptibility patterns may contribute to the empiric selection of therapy.

2 DOSAGE AND ADMINISTRATION

2.1 Important Administration Instructions

If a dose of Cefazolin for Injection and Dextrose Injection is required that does not equal 1 gram, 2 grams, or 3 grams, this product is not recommended for use and an alternative formulation of cefazolin should be considered.

Administer Cefazolin for Injection and Dextrose Injection intravenously over approximately 30 minutes.

2.2 Dosage for the Treatment of Infections

Dosage for the Treatment of Infections in Adults with Creatinine Clearance (CLcr) Equal to 55 mL/min or Greater

The recommended adult dosages for the treatment of infections [see Indications and Usage (1.1 to 1.8)] are outlined in Table 1 below. Administer Cefazolin for Injection and Dextrose Injection intravenously over approximately 30 minutes.

Table 1: Recommended Dosage in Adult Patients with CLcr Equal to 55 mL/min or Greater [If a dose of Cefazolin for Injection and Dextrose Injection is required that does not equal 1 gram, 2 grams, or 3 grams this product is not recommended for use and an alternative formulation of cefazolin should be considered.] .
Site and Type of Infection | Dose | Frequency
Moderate to severe infections | 500 mg to 1 gram | every 6 to 8 hours
Mild infections caused by susceptible gram-positive cocci | 250 mg to 500 mg | every 8 hours
Acute, uncomplicated urinary tract infections | 1 gram | every 12 hours
Pneumococcal pneumonia | 500 mg | every 12 hours
Severe, life-threatening infections (e.g., endocarditis, septicemia) [In rare instances, doses of up to 12 grams of cefazolin per day have been used.] | 1 gram to 1.5 grams | every 6 hours

Dosage for the Treatment of Infections in Pediatric Patients with CLcr Equal to 70 mL/min or Greater

The recommended pediatric dosages for the treatment of infections [see Indications and Usage (1.1 to 1.8)] are outlined in Table 2 below. Administer Cefazolin for Injection and Dextrose Injection intravenously over approximately 30 minutes.

If a dose of Cefazolin for Injection and Dextrose Injection is required that does not equal 1 gram, 2 grams or 3 grams, this product is not recommended for use and an alternative formulation of cefazolin should be considered [see Use in Specific Populations (8.4)].

Table 2: Recommended Dosage in Pediatric Patients with CLcr 70 mL/min or greater for Treatment of Infections [see Indications and Usage (1.1 to 1.8)]
Type of Severity | Recommended Total Daily Dosage
Mild to moderate infections | 25 mg/kg to 50 mg/kg, divided into 3 or 4 equal doses
Severe infections | May increase to 100 mg/kg, divided into 3 or 4 equal doses

2.3 Dosage for Perioperative Prophylaxis

Dosage for Perioperative Prophylaxis in Adults with CLcr Equal to 55 mL/min or Greater

To prevent postoperative infection in contaminated or potentially contaminated surgery, recommended dosages are described in Table 3 below.

Table 3: Recommended Dosage for Perioperative Prophylaxis in Adults with CLcr Equal to 55 mL/min or Greater
Body weight (kg) | Dose administered 1/2 hour to 1 hour prior to the start of surgery | Additional dose during lengthy operative procedures (e.g., 2 hours or more) | Dose for 24 hours postoperatively
Less than 120 kg | 1 gram to 2 grams | 500 mg to 1 gram | 500 mg to 1 gram every 6 hours to 8 hours
Greater than or equal to 120 kg | 3 grams | 500 mg to 1 gram | 500 mg to 1 gram every 6 hours to 8 hours

If a dose of Cefazolin for Injection and Dextrose Injection is required that does not equal 1 gram, 2 grams, or 3 grams, this product is not recommended and an alternative formulation of cefazolin should be considered.

It is important that (i) the preoperative dose be given just prior (1/2 hour to 1 hour) to the start of surgery so that adequate antibacterial concentrations are present in the serum and tissues at the time of initial surgical incision; and (ii) cefazolin be administered, if necessary, at appropriate intervals during surgery to provide sufficient concentrations of the antibacterial drug at the anticipated moments of greatest exposure to infective organisms.

The perioperative prophylactic administration of cefazolin should usually be discontinued within a 24-hour period after the surgical procedure. In surgery where the occurrence of infection may be particularly devastating (e.g., open-heart surgery and prosthetic arthroplasty), the prophylactic administration of cefazolin may be continued for 3 days to 5 days following the completion of surgery.

Dosage for Perioperative Prophylaxis in Pediatric Patients Aged 10 to 17 Years Old with CLcr 70 mL/min or Greater

To prevent postoperative infection in contaminated or potentially contaminated surgery, recommended doses are described in Table 4 below.

Table 4: Recommended Dosage for Perioperative Prophylaxis in Pediatric Patients with CLcr 70 mL/min or greater Aged 10 to 17 years Old [If a dose of Cefazolin for Injection and Dextrose Injection is required that does not equal 1 gram or 2 grams, this product is not recommended for use and an alternative formulation of cefazolin should be considered.]
Body weight (kg) | Dose administered 1/2 to 1 hour prior to the start of surgery | Additional dose during lengthy operative procedures (e.g., 2 hours or more) | Dose for 24 hours postoperatively
Less than 50 kg | 1 gram | 500 mg to 1 gram | 500 mg to 1 gram every 6 hours to 8 hours
Greater than or equal to 50 kg and less than 120 kg | 2 grams | 500 mg to 1 gram | 500 mg to 1 gram every 6 hours to 8 hours

It is important that (i) the preoperative dose be given just prior (1/2 hour to 1 hour) to the start of surgery so that adequate antibacterial concentrations are present in the serum and tissues at the time of initial surgical incision; and (ii) cefazolin be administered, if necessary, at appropriate intervals during surgery to provide sufficient concentrations of the antibacterial drug at the anticipated moments of greatest exposure to infective organisms.

The administration of Cefazolin for Injection and Dextrose Injection for perioperative prophylaxis should usually be discontinued within a 24-hour period after the surgical procedure. In surgery where the occurrence of infection may be particularly devastating the administration of Cefazolin for Injection and Dextrose Injection for perioperative prophylaxis may be continued for 3 days to 5 days following the completion of surgery.

2.4 Dosage Recommendations in Adult and Pediatric Patients with Renal Impairment

Dosage Recommendations in Adult Patients with CLcr less than 55 mL/min

The dosage recommendation for Cefazolin for Injection and Dextrose Injection in adult patients with renal impairment (CLcr less than 55 mL/min) is outlined in Table 5 below.

Table 5: Dosage Recommendation for Adult Patients with CLcr less than 55 mL/min
Creatinine Clearance | Dose | Frequency
35 to 54 mL/min | Recommended dose | every 8 hours or longer
11 to 34 mL/min | Half of recommended dose [If the recommended dose in adult patients with creatinine clearance equal to 35 mL/min or greater is 1 gram, then this product is not recommended for use in patients with creatinine clearance less than 35 mL/min and an alternative formulation of cefazolin should be considered.] | every 12 hours
10 mL/min or less | Half of recommended dose | every 18 to 24 hours

Dosage Recommendations in Pediatric Patients with CLcr less than 70 mL/min

The dosage recommendation for Cefazolin for Injection and Dextrose Injection in pediatric patients with renal impairment (CLcr less than 70 mL/min) is outlined in Table 6 below.

Table 6: Recommended Dosage in Pediatric Patients with CLcr less than 70 mL/min
Creatinine Clearance | Recommended Dosage
40 to 70 mL/min | 60% of the normal daily dose given in equally divided doses every 12 hours
20 to 40 mL/min | 25% of the normal daily dose given in equally divided doses every 12 hours
5 to 20 mL/min | 10% of the normal daily dose every 24 hours

*If a dose of Cefazolin for Injection and Dextrose Injection is required that does not equal 1 gram, 2 grams, or 3 grams, this product is not recommended for use and an alternative formulation of cefazolin should be considered.

2.5 Preparation for Use of Cefazolin for Injection and Dextrose Injection in DUPLEX® Container

This reconstituted solution of Cefazolin for Injection and Dextrose Injection is for intravenous use only.

Do not use plastic containers in series connections. Such use would result in air embolism due to residual air being drawn from the primary container before administration of the fluid from the secondary container is complete. If administration is controlled by a pumping device, care must be taken to discontinue pumping action before the container runs dry or air embolism may result.

Parenteral drug products should be inspected visually for particulate matter and discoloration prior
to administration. Use only if solution is clear and container and seals are intact.

DUPLEX® Container Storage

- To avoid inadvertent activation, the DUPLEX® Container should remain in the folded position until activation is intended.

Patient Labeling and Drug Powder/Diluent Inspection

- Apply patient-specific label on foil side of container. Use care to avoid activation. Do not cover any portion of foil strip with patient label.
- Unlatch side tab and unfold DUPLEX® Container (see Diagram 1).

- Visually inspect diluent chamber for particulate matter.
- Use only if container and seals are intact.
- To inspect the drug powder for foreign matter or discoloration, peel foil strip from drug chamber (see Diagram 2).

- Protect from light after removal of foil strip.

Note: If foil strip is removed, the container should be re-folded and the side tab latched until ready to activate. The product must then be used within 7 days, but not beyond the labeled expiration date.

Reconstitution (Activation)

- Do not use directly after storage by refrigeration, allow the product to equilibrate to room temperature before patient use.
- Unfold the DUPLEX® Container and point the set port in a downward direction. Starting at the hanger tab end, fold the DUPLEX® Container just below the diluent meniscus trapping all air above the fold. To activate, squeeze the folded diluent chamber until the seal between the diluent and powder opens, releasing diluent into the drug powder chamber (see Diagram 3).

- Agitate the liquid-powder mixture until the drug powder is completely dissolved.

Note: Following reconstitution (activation), product must be used within 24 hours if stored at room temperature or within 7 days if stored under refrigeration.

Administration

- Visually inspect the reconstituted solution for particulate matter.
- Point the set port in a downwards direction. Starting at the hanger tab end, fold the DUPLEX® Container just below the solution meniscus trapping all air above the fold. Squeeze the folded DUPLEX® Container until the seal between reconstituted drug solution and set port opens, releasing liquid to set port (see Diagram 4).

- Prior to attaching the IV set, check for minute leaks by squeezing container firmly. If leaks are found, discard container and solution as sterility may be compromised.
- Using aseptic technique, peel foil cover from the set port and attach sterile administration set (see Diagram 5).

- Refer to directions for use accompanying the administration set.

Important Administration Instructions

- Do not use in series connections.
- Do not introduce additives into the DUPLEX® Container.
- Administer Cefazolin for Injection and Dextrose Injection intravenously over approximately 30 minutes.

3 DOSAGE FORMS AND STRENGTHS

Dual-chamber, single-dose packaged combination of Cefazolin Sodium USP (lyophilized) and sterile iso-osmotic diluent in the DUPLEX® sterile container consisting of:

- 1 gram Cefazolin for Injection USP and 50 mL 4% Dextrose Injection USP
- 2 grams Cefazolin for Injection USP and 50 mL 3% Dextrose Injection USP
- 3 grams Cefazolin for Injection USP and 50 mL 2% Dextrose Injection USP

4 CONTRAINDICATIONS

4.1 Hypersensitivity to Cefazolin or the Cephalosporin Class of Antibacterial Drugs, Penicillins, or Other Beta-lactams

Cefazolin for Injection and Dextrose Injection is contraindicated in patients who have a history of immediate hypersensitivity reactions (e.g., anaphylaxis, serious skin reactions) to cefazolin or the cephalosporin class of antibacterial drugs, penicillins, or other beta-lactams [see Warnings and Precautions (5.1)].

5 WARNINGS AND PRECAUTIONS

5.1 Hypersensitivity Reactions to Cefazolin, Cephalosporins, Penicillins, or Other Beta-lactams

Serious and occasionally fatal hypersensitivity (anaphylactic) reactions have been reported in patients receiving beta-lactam antibacterial drugs. Before therapy with Cefazolin for Injection and Dextrose Injection is instituted, careful inquiry should be made to determine whether the patient has had previous immediate hypersensitivity reactions to cefazolin, cephalosporins, penicillins, or carbapenems. Exercise caution if this product is to be given to penicillin-sensitive patients because cross-hypersensitivity among beta-lactam antibacterial drugs has been clearly documented and may occur in up to 10% of patients with a history of penicillin allergy. If an allergic reaction to Cefazolin for Injection and Dextrose Injection occurs, discontinue the drug.

5.2 Seizures in Patients with Renal Impairment

Seizures may occur with the administration of Cefazolin for Injection and Dextrose Injection, particularly in patients with renal impairment when the dosage is not reduced appropriately. Discontinue Cefazolin for Injection and Dextrose Injection if seizures occur or make appropriate dosage adjustments in patients with renal impairment [see Dosage and Administration (2.4)]. Anticonvulsant therapy should be continued in patients with known seizure disorders.

5.3 Clostridioides difficile-associated Diarrhea

Clostridioides difficile-associated diarrhea (CDAD) has been reported with use of nearly all antibacterial agents, including cefazolin, and may range in severity from mild diarrhea to fatal colitis. Treatment with antibacterial agents alters the normal flora of the colon leading to overgrowth of C. difficile.
C. difficile produces toxins A and B, which contribute to the development of CDAD. Hypertoxin-producing isolates of C. difficile cause increased morbidity and mortality, as these infections can be refractory to antimicrobial therapy and may require colectomy. CDAD must be considered in all patients who present with diarrhea following antibacterial drug use. Careful medical history is necessary since CDAD has been reported to occur over two months after the administration of antibacterial agents.

If CDAD is suspected or confirmed, ongoing antibacterial drug use not directed against C. difficile may need to be discontinued. Appropriate fluid and electrolyte management, protein supplementation, antibacterial drug treatment of C. difficile, and surgical evaluation should be instituted as clinically indicated.

5.4 Hypersensitivity to Dextrose-containing Products

Hypersensitivity reactions, including anaphylaxis, have been reported with administration of dextrose-containing products. These reactions have been reported in patients receiving high concentrations of dextrose (i.e. 50% dextrose)^1. The reactions have also been reported when corn-derived dextrose solutions were administered to patients with or without a history of hypersensitivity to corn products.^2

5.5 Prothrombin Activity

Cefazolin for Injection and Dextrose Injection may be associated with a fall in prothrombin activity. Those at risk include patients with renal or hepatic impairment or poor nutritional state, as well as patients receiving a protracted course of antimicrobial therapy, and patients previously stabilized on anticoagulant therapy. Prothrombin time should be monitored in patients at risk and exogenous vitamin K administered as indicated.

5.6 Risk of Development of Drug-resistant Bacteria

Prescribing Cefazolin for Injection and Dextrose Injection in the absence of proven or strongly suspected bacterial infection or a prophylactic indication is unlikely to provide benefit to the patient and increases the risk of the development of drug-resistant bacteria.

As with other antimicrobials, prolonged use of Cefazolin for Injection and Dextrose Injection may result in overgrowth of nonsusceptible microorganisms. Repeated evaluation of the patient's condition is essential. Should superinfection occur during therapy, appropriate measures should be taken.

5.7 Drug/Laboratory Test Interactions

Urinary Glucose

The administration of cefazolin may result in a false-positive reaction with glucose in the urine when using glucose tests based on Benedict’s copper reduction reaction that determine the amount of reducing substances like glucose in the urine. It is recommended that glucose tests based on enzymatic glucose oxidase be used.

Coombs’ Test

Positive direct Coombs' tests have been reported during treatment with cefazolin. In hematologic studies or in transfusion cross-matching procedures when antiglobulin tests are performed on the minor side or in Coombs' testing of newborns whose mothers have received cephalosporin antibacterial drugs before parturition, it should be recognized that a positive Coombs' test may be due to the drug.

5.8 Patients with Overt or Known Subclinical Diabetes Mellitus or Carbohydrate Intolerance

As with other dextrose-containing solutions, Cefazolin for Injection and Dextrose Injection should be prescribed with caution in patients with overt or known subclinical diabetes mellitus or carbohydrate intolerance for any reason.

6 ADVERSE REACTIONS

The following serious adverse reactions to Cefazolin for Injection and Dextrose Injection are described below and elsewhere in the labeling:

- Hypersensitivity Reactions to Cefazolin, Cephalosporins, Penicillins, or Other Beta-lactams [see Warnings and Precautions (5.1)]
- Seizures in Patients with Renal Impairment [see Warnings and Precautions (5.2)]
- Clostridioides difficile-associated Diarrhea [see Warnings and Precautions (5.3)]
- Prothrombin Activity [see Warnings and Precautions (5.5)]

6.1 Clinical Trials Experience

Because clinical trials are conducted under widely varying conditions, adverse reaction rates observed in the clinical trials of a drug cannot be directly compared to rates in the clinical trials of another drug and may not reflect the rates observed in practice.

The following adverse reactions were reported from clinical trials:

Gastrointestinal: Diarrhea, oral candidiasis (oral thrush), mouth ulcers, vomiting, nausea, stomach cramps, epigastric pain, heartburn, flatus, anorexia and pseudomembranous colitis. Onset of pseudomembranous colitis symptoms may occur during or after antibacterial treatment [see Warnings and Precautions (5.3)].

Allergic: Anaphylaxis, eosinophilia, urticaria, itching, drug fever, skin rash, Stevens-Johnson syndrome.

Hematologic: Neutropenia, leukopenia, thrombocytopenia, thrombocythemia.

Hepatic: Transient rise in SGOT, SGPT, and alkaline phosphatase levels has been observed. Reports of hepatitis have been received.

Renal: Reports of increased BUN and creatinine levels, as well as renal failure, have been received.

Local Reactions: Instances of phlebitis have been reported at site of injection. Some induration has occurred.

Other Reactions: Pruritus (including genital, vulvar and anal pruritus, genital moniliasis, and vaginitis). Dizziness, fainting, lightheadedness, confusion, weakness, tiredness, hypotension, somnolence and headache.

Adverse Reactions in Pediatric Patients for Perioperative Prophylaxis

Two studies (Study 1: NCT 3231228 and Study 2: NCT 01904357) were conducted to assess the safety and pharmacokinetics of a single 30-minute infusion of either 1 gram or 2 grams (based on weight) of Cefazolin for Injection and Dextrose Injection for perioperative prophylaxis in pediatric patients.

Study 1 was a multicenter, open-label, non-comparative, parallel group study to evaluate the safety and pharmacokinetics of a single 30-minute infusion of either 1 gram or 2 grams (based on weight) of Cefazolin for Injection and Dextrose Injection for perioperative prophylaxis in 61 pediatric patients 10 to 17 years of age. Thirty-three subjects with a weight of at least 25 kg but less than 60 kg received a single-dose of 1 gram of cefazolin and 28 subjects with a weight of at least 60 kg received a single-dose of 2 grams of cefazolin. The mean age of the safety population was 14 years and ranged from 10 to 17 years. There were no adverse reactions leading to study discontinuation or deaths reported during the study. The most frequently reported adverse reactions were nausea (14.8%), infusion site pain (6.6%), and headache (4.9%).

Study 2 was a multicenter, non-comparative study that evaluated the safety and pharmacokinetics of a single 30-minute infusion of either 1 gram or 2 grams (based on weight) of Cefazolin for Injection and Dextrose Injection for perioperative prophylaxis in 12 pediatric patients 10 to 12 years of age. Subjects weighing at least 25 kg to less than 50 kg received a single-dose of 1 gram of Cefazolin for Injection and Dextrose Injection and subjects weighing at least 50 kg to less than 85 kg received a single-dose of 2 grams of Cefazolin for Injection and Dextrose Injection.

The safety findings in Study 2 in pediatric patients aged 10 to 12 years old were similar to those observed in adult patients and the pediatric patients aged 10 to 17 years old in Study 1.

6.2 Postmarketing Experience

The following adverse reactions have been identified during post approval use of cefazolin. Because these reactions are reported voluntarily from a population of uncertain size, it is not always possible to reliably estimate their frequency or establish a causal relationship to drug exposure.

Immune system disorders: Serum sickness-like reaction

Renal and urinary disorders: Acute tubulointerstitial nephritis (ATIN)

Skin and subcutaneous tissue disorders: Acute generalized exanthematous pustulosis (AGEP)

6.3 Cephalosporin-class Adverse Reactions

In addition to the adverse reactions listed above that have been observed in patients treated with cefazolin, the following adverse reactions and altered laboratory tests have been reported for cephalosporin-class antibacterials:

Stevens-Johnson syndrome, erythema multiforme, toxic epidermal necrolysis, renal impairment, toxic nephropathy, aplastic anemia, hemolytic anemia, hemorrhage, a fall in prothrombin activity, hepatic impairment including cholestasis, and pancytopenia.

7 DRUG INTERACTIONS

The renal excretion of cefazolin is inhibited by probenecid. Co-administration of probenecid with Cefazolin for Injection and Dextrose Injection is not recommended.

8 USE IN SPECIFIC POPULATIONS

8.1 Pregnancy

Risk Summary

Available data from published prospective cohort studies, case series and case reports over several decades with cephalosporin use, including cefazolin, in pregnant women have not established a drug-associated risk of major birth defects, miscarriage, or adverse maternal or fetal outcomes. Cefazolin crosses the placenta.

Animal reproduction studies with rats, mice and rabbits administered cefazolin during organogenesis at doses 1 to 3 times the maximum recommended human dose (MRHD) did not demonstrate adverse developmental outcomes. In rats subcutaneously administered cefazolin prior to delivery and throughout lactation, there were no adverse effects on offspring at a dose approximately 2 times the MRHD (see Data).

The estimated background risk of major birth defects and miscarriage for the indicated population is unknown. All pregnancies have a background risk of birth defect, loss, or other adverse outcomes. In the U.S. general population, the estimated background risk of major birth defects and miscarriage in clinically recognized pregnancies is 2% to 4% and 15% to 20%, respectively.

Data

Human Data

While available studies cannot definitively establish the absence of risk, published data from case-control studies and case reports over several decades have not identified an association with cephalosporin use during pregnancy and major birth defects, miscarriage, or other adverse maternal or fetal outcomes. Available studies have methodologic limitations, including small sample size, retrospective data collection, and inconsistent comparator groups.

Animal Data

Reproduction studies have been performed in rats, mice and rabbits administered cefazolin during organogenesis at doses of 2000, 4000 and 240 mg/kg/day (approximately 1 to 3 times the maximum recommended human dose on a body surface area comparison). There was no evidence of any adverse effects on embryofetal development due to cefazolin. In a peri-postnatal study in rats, cefazolin administered subcutaneously up to 1200 mg/kg/day (approximately 2 times the MRHD based on body surface area comparison) to pregnant dams prior to delivery and through lactation caused no adverse effects on offspring.

8.2 Lactation

Data from published literature report that cefazolin is present in human milk, but is not expected to accumulate in a breastfed infant. There are no data on the effects of cefazolin on the breastfed child or on milk production.

The developmental and health benefits of breastfeeding should be considered along with the mother’s clinical need for Cefazolin for Injection and Dextrose Injection and any potential adverse effects on the breastfed child from Cefazolin for Injection and Dextrose Injection or from the mother’s underlying condition.

8.4 Pediatric Use

Cefazolin for Injection and Dextrose Injection is indicated for the treatment of respiratory tract infections, urinary tract infections, skin and skin structure infections, biliary tract infections, bone and joint infections, genital infections, septicemia, and endocarditis in pediatric patients for whom appropriate dosing with this formulation can be achieved, and for perioperative prophylaxis in pediatric patients aged 10 to 17 years old [see Indications and Usage (1.1 to 1.9)].

Safety and effectiveness of Cefazolin for Injection and Dextrose Injection in premature infants and neonates have not been established and is not recommended for use in this age group of pediatric patients. Dosing for cefazolin in pediatric patients younger than one month old has not been established.

Because of the limitations of the available strengths and administration requirements (i.e., administration of fractional doses is not recommended) of Cefazolin for Injection and Dextrose Injection, and to avoid unintentional overdose, this product is not recommended for use if a dose of Cefazolin for Injection and Dextrose Injection that does not equal 1 gram or 2 grams is required and an alternative formulation of cefazolin should be considered [see Dosage and Administration (2.2, 2.3, 2.4 and 2.5)].

The safety and effectiveness of Cefazolin for Injection and Dextrose Injection for perioperative prophylaxis have been established in pediatric patients aged 10 to 17 years old. Use of Cefazolin for Injection and Dextrose Injection in these age groups is supported by evidence from adults with additional safety and pharmacokinetic data in pediatric patients aged 10 to 17 years old. Safety and pharmacokinetics were evaluated in two multicenter, non-comparative studies (Study 1 and Study 2). These studies were conducted to assess the safety and pharmacokinetics of a single 30-minute infusion of either 1 gram or 2 grams (based on weight) of Cefazolin for Injection and Dextrose Injection for perioperative prophylaxis in pediatric patients. Study 1 evaluated the safety and pharmacokinetics of 1 gram of Cefazolin for Injection and Dextrose Injection in pediatric patients aged 10 to 17 years old scheduled for surgery with a weight of at least 25 kg but less than 60 kg and, 2 grams in pediatric patients with a weight of at least 60 kg. Study 2 evaluated 1 gram of Cefazolin for Injection and Dextrose Injection in pediatric patients aged 10 to 12 years old scheduled for surgery with a weight of at least 25 kg but less than 50 kg and, 2 grams in pediatric patients with a weight of at least 50 kg to less than 85 kg [see Dosage and Administration (2.3), Adverse Reactions (6.1) and Clinical Pharmacology (12.3)].

The safety and effectiveness of Cefazolin for Injection and Dextrose Injection for perioperative prophylaxis have not been established in pediatric patients younger than 10 years old.

8.5 Geriatric Use

Of the 920 subjects who received cefazolin in clinical studies, 313 (34%) were 65 years and over, while 138 (15%) were 75 years and over. No overall differences in safety or effectiveness were observed between these subjects and younger subjects. Other reported clinical experience has not identified differences in responses between the elderly and younger patients, but greater sensitivity of some older individuals cannot be ruled out.

This drug is known to be substantially excreted by the kidney, and the risk of toxic reactions to this drug may be greater in patients with impaired renal function. Because elderly patients are more likely to have decreased renal function, care should be taken in dose selection, and it may be useful to monitor renal function [see Dosage and Administration (2.4) and Warnings and Precautions (5.2)].

8.6 Patients with Renal Impairment

When Cefazolin for Injection and Dextrose Injection is administered to adult and pediatric patients with low urinary output because of impaired renal function (creatinine clearance less than 55 mL/min and 70 mL/min for adults and pediatric patients, respectively), lower daily dosage is required [see Dosage and Administration (2.4) and Warnings and Precautions (5.2)].

10 OVERDOSAGE

Accidental overdosage resulting in seizures may occur in patients with renal impairment who receive doses greater than the recommended dosage of Cefazolin for Injection and Dextrose Injection [see Warnings and Precautions (5.2)]. If seizures associated with accidental overdosage occur, discontinue Cefazolin for Injection and Dextrose Injection and give supportive treatment.

11 DESCRIPTION

Cefazolin for Injection USP and Dextrose Injection USP is a sterile, nonpyrogenic, single-dose, packaged combination of Cefazolin Sodium USP (lyophilized) and sterile iso-osmotic diluent in the DUPLEX® sterile container. The DUPLEX® Container is a flexible dual chamber container.

After reconstitution the approximate osmolality for Cefazolin for Injection USP and Dextrose Injection USP is 290 mOsmol/kg.

The drug chamber is filled with sterile lyophilized Cefazolin Sodium USP, a semi-synthetic cephalosporin and has the following IUPAC nomenclature: Sodium (6R,7R)-3-[[(5-methyl-1,3,4-thiadiazol-2-yl)thio]methyl]-8-oxo-7-[2-(1H-tetrazol-1-yl)acetamido]-5-thia-1-azabicyclo[4.2.0]oct-2-ene-2-carboxylate. Its empirical formula is C14H13N8NaO4S3 and its molecular weight is 476.48.

Cefazolin Sodium USP has the following structural formula:

The sodium content is 48 mg/g of cefazolin sodium.

The diluent chamber contains Dextrose Injection USP, an iso-osmotic diluent using Hydrous Dextrose USP in Water for Injection USP. Dextrose Injection USP is sterile, nonpyrogenic, and contains no bacteriostatic or antimicrobial agents. Its empirical formula is C6H12O6•H2O and its molecular weight is 198.17.

Hydrous Dextrose USP has the following structural (molecular) formula:

Cefazolin Sodium USP is supplied as a lyophilized form equivalent to either 1 gram, 2 grams or 3 grams of cefazolin. The 1 gram / container Cefazolin Sodium USP contains 1 gram of cefazolin (equivalent to 1.048 grams of cefazolin sodium). The 2 grams / container Cefazolin Sodium USP contains 2 grams of cefazolin (equivalent to 2.096 grams of cefazolin sodium). The 3 grams / container Cefazolin Sodium USP contains 3 grams of cefazolin (equivalent to 3.145 grams of cefazolin sodium). Dextrose Hydrous USP has been added to the diluent (Water for Injection USP) to adjust osmolality (approximately 2 grams [4% w/v], 1.5 grams [3% w/v] and 1 gram [2% w/v] for the 1 gram, 2 gram or 3 gram dosages, respectively).

After removing the peelable foil strip, activating the seals, and thoroughly mixing, the reconstituted drug product is intended for single intravenous use.

The pH of reconstituted solutions of Cefazolin for Injection and Dextrose Injection is 3.5 to 7.0.

Reconstituted solutions of Cefazolin for Injection and Dextrose Injection range in color from pale yellow to amber.

Not made with natural rubber latex, PVC or DEHP.

The DUPLEX® dual chamber container is made from a specially formulated material. The product (diluent and drug) contact layer is a mixture of thermoplastic rubber and a polypropylene ethylene copolymer that contains no plasticizers. The safety of the container system is supported by USP biological evaluation procedures.

12 CLINICAL PHARMACOLOGY

12.1 Mechanism of Action

Cefazolin is an antibacterial drug [see Microbiology (12.4)].

12.2 Pharmacodynamics

The pharmacokinetic/pharmacodynamic relationship for cefazolin has not been evaluated in patients.

12.3 Pharmacokinetics

Studies have shown that following intravenous administration of cefazolin to normal volunteers, mean serum concentrations peaked at approximately 185 mcg/mL and were approximately 4 mcg/mL at 8 hours for a 1 gram dose.

The serum half-life for cefazolin is approximately 1.8 hours following IV administration.

In a study of constant intravenous infusion with dosages of 3.5 mg/kg for 1 hour (approximately 250 mg) and 1.5 mg/kg the next 2 hours (approximately 100 mg) in healthy volunteers, cefazolin serum concentrations at the third hour were approximately 28 mcg/mL.

Plasma pharmacokinetic parameters of cefazolin in healthy volunteers (N=12) following a single 15-minute IV infusion of 2 grams of Cefazolin for Injection and Dextrose Injection are summarized in Table 7.

Table 7: Mean (Standard Deviation) Plasma Pharmacokinetic Parameters of Cefazolin in Healthy Volunteers
Dosage of Cefazolin for Injection and Dextrose Injection | N | Cmax; (mcg/mL) | Tmax [Tmax reported as median (range)] (h) | AUC0-inf (mcg*h/mL) | t1/2 (h) | CL (L/h) | Vz (L)
Single 2 grams Dose as a 15-Minute IV Infusion | 12 | 280.9 (45.9) | 0.25 (0.25-0.33) | 509.9 (89.3) | 2.01 (0.28) | 4.03 (0.68) | 11.50 (1.53)

N= number of subjects observed; Cmax = maximum plasma concentration; Tmax = time to maximum plasma concentration; AUC0-inf = area under the plasma concentration-time curve extrapolated to infinity; t1/2 = apparent plasma terminal elimination half-life; CL = total clearance; Vz = volume of distribution

Model derived plasma pharmacokinetic parameters of cefazolin in adult patients weighing 120 kg or greater (N=12) following a single 30-minute IV infusion of 3 grams of Cefazolin for Injection and Dextrose Injection are summarized in Table 8.

Table 8: Mean (Standard Deviation) Model Derived Plasma Pharmacokinetic
Parameters of Cefazolin in Adult Patients Weighing ≥ 120 kg
Dosage of Cefazolin for Injection and Dextrose Injection | N | Cmax (mcg/mL) | Tmax (h) | AUC0--inf (mcg*h/mL) | t1/2 (h) | CL (L/h) | Vz (L)
Single 3 grams Dose as a 30-Minute IV Infusion | 12 | 197.7 (46.6) | 0.5 | 598.6 (206.6) | 2.36 (0.687) | 5.52 (1.72) | 17.51 (3.63)

* Tmax reported based on infusion duration

N= number of subjects observed; Cmax = maximum plasma concentration; Tmax = time to maximum plasma concentration; AUC0-inf = area under the plasma concentration-time curve extrapolated to infinity; t1/2 = apparent plasma terminal elimination half-life; CL = total clearance; Vz = volume of distribution

Studies in patients hospitalized with infections indicate that cefazolin mean peak serum concentrations were approximately equivalent to those seen in healthy volunteers.

Bile concentrations in patients without obstructive biliary disease can reach or exceed serum concentrations by up to five times; however, in patients with obstructive biliary disease, bile concentrations of cefazolin are considerably lower than serum concentrations (less than 1.0 mcg/mL).

In synovial fluid, the cefazolin concentration becomes comparable to that reached in serum at about 4 hours after drug administration.

Studies of cord blood show prompt transfer of cefazolin across the placenta. Cefazolin is present in very low concentrations in the milk of nursing mothers.

Cefazolin is excreted unchanged in the urine. In the first 6 hours, approximately 60% of the drug is excreted in the urine and this increases to 70% to 80% within 24 hours.

Specific Populations

Pediatric Patients for Perioperative Prophylaxis

A simulation based on pharmacokinetic data from healthy adults (n=24), pediatric patients aged 10 to 17 years (n=26: Study 1 [see Adverse Reactions (6.1)]), and pediatric patients aged 10 to 12 years (n=12: Study 2 [see Adverse Reactions (6.1)] indicate that the administration of a 1 gram cefazolin dose for pediatric patients weighing less than 50 kg and a 2 gram cefazolin dose for those weighing 50 kg or greater will provide comparable exposures between pediatric patients aged 10 to 17 years and healthy adults receiving 2 grams Cefazolin for Injection and Dextrose Injection [see Dosage and Administration (2.2 and 2.3) and Use in Specific Populations (8.4)].

12.4 Microbiology

Mechanism of Action

Cefazolin is a bactericidal agent that acts by inhibition of bacterial cell wall synthesis.

Resistance

Predominant mechanisms of bacterial resistance to cephalosporins include the presence of extended-spectrum beta-lactamases and enzymatic hydrolysis.

Antimicrobial Activity

Cefazolin has been shown to be active against most isolates of the following microorganisms, both in vitro and in clinical infections [see Indications and Usage (1)].

Gram-positive bacteria

- Staphylococcus aureus
- Staphylococcus epidermidis
- Streptococcus agalactiae
- Streptococcus pneumoniae
- Streptococcus pyogenes

Methicillin-resistant staphylococci are uniformly resistant to cefazolin.

Gram-negative bacteria

- Escherichia coli
- Proteus mirabilis

Most isolates of indole positive Proteus (Proteus vulgaris), Enterobacter spp., Morganella morganii, Providencia rettgeri, Serratia spp., and Pseudomonas spp. are resistant to cefazolin.

Susceptibility Testing

For specific information regarding susceptibility test interpretive criteria, and associated test methods and quality control standards recognized by FDA for this drug, please see: http://www.fda.gov/STIC.

13 NONCLINICAL TOXICOLOGY

13.1 Carcinogenesis, Mutagenesis, Impairment of Fertility

Carcinogenicity and Mutagenesis

Mutagenicity studies and long-term studies in animals to determine the carcinogenic potential of Cefazolin for Injection and Dextrose Injection have not been performed.

Impairment of Fertility

Fertility studies conducted in rats subcutaneously administered cefazolin at doses of 2000 mg/kg/day (approximately 3 times the maximum recommended human dose based on body surface area comparison) showed no impairment of mating and fertility.

15 REFERENCES

1. Czarny D, Prichard PJ, Fennessy M, Lewis S. Anaphylactoid reaction to 50% solution of dextrose. Med J Aust 1980;2:255-258.
2. Guharoy, SR, Barajas M. Probably Anaphylactic Reaction to Corn-Derived Dextrose Solution. Vet Hum Toxicol 1991;33:609-610.

16 HOW SUPPLIED/STORAGE AND HANDLING

Cefazolin for Injection USP and Dextrose Injection USP in the single-dose DUPLEX® Container is a flexible dual chamber container supplied in three concentrations. After reconstitution, the concentrations are equivalent to either 1 gram, 2 grams or 3 grams of cefazolin. The diluent chamber contains approximately 50 mL of Dextrose Injection USP. Dextrose Injection USP has been adjusted to 4%, 3% and 2% for the 1 gram, 2 gram and 3 gram doses, respectively, such that the reconstituted solution is iso-osmotic.

Cefazolin for Injection USP and Dextrose Injection USP is supplied sterile and nonpyrogenic in the DUPLEX® Container packaged 24 units per case.

NDC | REF | Dose | Volume
0264-3103-11 | 3103-11 | 1 gram | 50 mL
0264-3105-11 | 3105-11 | 2 grams | 50 mL
0264-3107-11 | 3107-11 | 3 grams | 50 mL

Store the unactivated unit at 20-25°C (68-77°F). Excursions permitted to 15-30°C (59-86°F). [See USP Controlled Room Temperature.] Do not freeze.

As with other cephalosporins, reconstituted Cefazolin for Injection USP and Dextrose Injection USP tends to darken depending on storage conditions, within the stated recommendations. However, product potency is not adversely affected.

Use only if prepared solution is clear and free from particulate matter [see Dosage and Administration (2.5)].

17 PATIENT COUNSELING INFORMATION

Serious Allergic Reactions

Advise patients that allergic reactions, including serious allergic reactions could occur and that serious reactions require immediate treatment and discontinuation of Cefazolin for Injection and Dextrose Injection. Patients should report to their health care provider any previous allergic reactions to cefazolin, cephalosporins, penicillins, or other similar antibacterials [see Warnings and Precautions (5.1)].

Seizures

Advise patients that seizures could occur with Cefazolin for Injection and Dextrose Injection. Instruct patients to inform a healthcare provider at once of any signs and symptoms of seizures, for immediate treatment, dosage adjustment, or discontinuation of Cefazolin for Injection and Dextrose Injection [see Warnings and Precautions (5.2)].

Diarrhea

Advise patients that diarrhea is a common problem caused by antibacterials, including Cefazolin for Injection and Dextrose Injection, which usually ends when the antibacterial is discontinued. Sometimes after starting treatment with antibacterials, patients can develop watery and bloody stools (with or without stomach cramps and fever) even as late as two or more months after having taken the last dose of the antibacterials. If this occurs, patients should contact a physician as soon as possible [see Warnings and Precautions (5.3)].

Antibacterial Resistance

Patients should be counseled that antibacterial drugs, including Cefazolin for Injection and Dextrose Injection should only be used to treat bacterial infections. They do not treat viral infections (e.g., the common cold). When Cefazolin for Injection and Dextrose Injection is prescribed to treat a bacterial infection, patients should be told that although it is common to feel better early in the course of therapy, the medication should be taken exactly as directed. Skipping doses or not completing the full course of therapy may (1) decrease the effectiveness of the immediate treatment and (2) increase the likelihood that bacteria will develop resistance and will not be treatable by Cefazolin for Injection and Dextrose Injection or other antibacterial drugs in the future.

DUPLEX is a registered trademark of B. Braun Medical Inc.
ATCC is a registered trademark of the American Type Culture Collection.

B. Braun Medical Inc.
Bethlehem, PA 18018-3524 USA
1-800-227-2862

Prepared in USA.
API from USA and Italy.

Y36-003-090 LD-105-12

PRINCIPAL DISPLAY PANEL - 1g Cefazolin

Cefazolin for Injection USP
and Dextrose Injection USP

1g*
50 mL

REF 3103-11
NDC 0264-3103-11

DUPLEX® CONTAINER

Use only after mixing contents of both chambers.
For IV Use Only Iso-osmotic Single-Dose Sterile/Nonpyrogenic
* Contains 1.048 g of Cefazolin Sodium USP equivalent to 1 g cefazolin.

Reconstitution: Hold container with set port in a downward direction and fold
the diluent chamber just below the solution meniscus. To activate seal, squeeze
folded diluent chamber until seal between diluent and drug chamber opens,
releasing diluent into drug chamber. Agitate the reconstituted solution until the
drug powder is completely dissolved. Fold the container a second time and
squeeze until seal between drug chamber and set port opens.

After reconstitution each 50 mL single-dose unit contains: Cefazolin for Injection
USP (1 g cefazolin, equivalent to 1.048 g of cefazolin sodium) with approx. 2 g
(4% w/v) Hydrous Dextrose USP in Water for Injection USP.
Approximate osmolality: 290 mOsmol/kg

Prior to Reconstitution: Store at 20-25°C (68-77°F). Excursions permitted to
15-30°C (59-86°F). [See USP Controlled Room Temperature.] Use only if container
and seals are intact. Do not peel foil strip until ready for use. After foil strip
removal, product must be used within 7 days, but not beyond the labeled
expiration date. Protect from light after removal of foil strip.

After Reconstitution: Use only if prepared solution is clear and free from
particulate matter. Use within 24 hours if stored at room temperature or within
7 days if stored under refrigeration. Do not use in a series connection. Do not
introduce additives into this container. Prior to administration check for minute
leaks by squeezing container firmly. If leaks are found, discard container and
solution as sterility may be impaired. Do not freeze. Discard unused portion.

Not made with natural rubber latex, PVC or DEHP.

Rx only

B. Braun Medical Inc.
Bethlehem, PA 18018-3524

Prepared in USA. API from USA and Italy.

LD-201-9
Y37-002-610

EXP
LOT

PEEL HERE

Drug Chamber
Discard unit if foil strip is damaged. Peel foil strip only when
ready for use. Visually inspect drug prior to reconstitution.
See package insert for complete directions for reconstitution
and administration.
LD-336-1 X27-001-485

PRINCIPAL DISPLAY PANEL - 2g Cefazolin

Cefazolin for Injection USP
and Dextrose Injection USP

2g*
50 mL

REF 3105-11
NDC 0264-3105-11

DUPLEX® CONTAINER

Use only after mixing contents of both chambers.
For IV Use Only Iso-osmotic Single-Dose Sterile/Nonpyrogenic
* Contains 2.096 g of Cefazolin Sodium USP equivalent to 2 g cefazolin.

Reconstitution: Hold container with set port in a downward direction and fold
the diluent chamber just below the solution meniscus. To activate seal, squeeze
folded diluent chamber until seal between diluent and drug chamber opens,
releasing diluent into drug chamber. Agitate the reconstituted solution until the
drug powder is completely dissolved. Fold the container a second time
and squeeze until seal between drug chamber and set port opens.

After reconstitution each 50 mL single-dose unit contains: Cefazolin for Injection
USP (2 g cefazolin, equivalent to 2.096 g of cefazolin sodium) with approx. 1.5 g
(3% w/v) Hydrous Dextrose USP in Water for Injection USP.
Approximate osmolality: 290 mOsmol/kg

Prior to Reconstitution: Store at 20-25°C (68-77°F). Excursions permitted to
15-30°C (59-86°F). [See USP Controlled Room Temperature.] Use only if container
and seals are intact. Do not peel foil strip until ready for use. After foil strip
removal, product must be used within 7 days, but not beyond the labeled
expiration date. Protect from light after removal of foil strip.

After Reconstitution: Use only if prepared solution is clear and free from
particulate matter. Use within 24 hours if stored at room temperature or within
7 days if stored under refrigeration. Do not use in a series connection. Do not
introduce additives into this container. Prior to administration check for minute
leaks by squeezing container firmly. If leaks are found, discard container and
solution as sterility may be impaired. Do not freeze. Discard unused portion.
Not made with natural rubber latex, PVC or DEHP.

Rx only

B. Braun Medical Inc.
Bethlehem, PA 18018-3524

Prepared in USA. API from USA and Italy.

LD-200-6
Y37-002-611

EXP
LOT

PEEL HERE

Drug Chamber
Discard unit if foil strip is damaged. Peel foil strip only when
ready for use. Visually inspect drug prior to reconstitution.
See package insert for complete directions for reconstitution
and administration.
LD-336-1 X27-001-485

PRINCIPAL DISPLAY PANEL - 3g Cefazolin

Cefazolin for Injection USP
and Dextrose Injection USP

3g*
50 mL

REF 3107-11
NDC 0264-3107-11

DUPLEX® CONTAINER

Use only after mixing contents of both chambers.
For IV Use Only Iso-osmotic Single-Dose Sterile/Nonpyrogenic
* Contains 3.145 g of Cefazolin Sodium USP equivalent to 3 g of cefazolin.

Reconstitution: Hold container with set port in a downward direction and fold
the diluent chamber just below the solution meniscus. To activate seal, squeeze
folded diluent chamber until seal between diluent and drug chamber opens,
releasing diluent into drug chamber. Agitate the reconstituted solution until the
drug powder is completely dissolved. Fold the container a second time and
squeeze until seal between drug chamber and set port opens.

After reconstitution each 50 mL single-dose unit contains: Cefazolin for Injection
USP (3 g cefazolin, equivalent to 3.145 g of cefazolin sodium) with approx. 1 g
(2% w/v) Hydrous Dextrose USP in Water for Injection USP.
Approximate osmolality: 290 mOsmol/kg

Prior to Reconstitution: Store at 20-25°C (68-77°F). Excursions permitted to
15-30°C (59-86°F). [See USP Controlled Room Temperature.] Use only if container
and seals are intact. Do not peel foil strip until ready for use. After foil strip
removal, product must be used within 7 days, but not beyond the labeled
expiration date. Protect from light after removal of foil strip.

After Reconstitution: Use only if prepared solution is clear and free from
particulate matter. Use within 24 hours if stored at room temperature or within
7 days if stored under refrigeration. Do not use in a series connection. Do not
introduce additives into this container. Prior to administration check for minute
leaks by squeezing container firmly. If leaks are found, discard container and
solution as sterility may be impaired. Do not freeze. Discard unused portion.
Not made with natural rubber latex, PVC or DEHP.

Rx only

B. Braun Medical Inc.
Bethlehem, PA 18018-3524
Prepared in USA. API from USA and Italy.

LD-792-2
Y37-002-609

EXP
LOT

PEEL HERE

Drug Chamber
Discard unit if foil strip is damaged. Peel foil strip only when
ready for use. Visually inspect drug prior to reconstitution.
See package insert for complete directions for reconstitution
and administration.
LD-336-1 X27-001-485